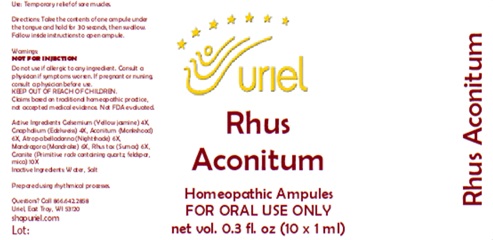 DRUG LABEL: Rhus Aconitum
NDC: 48951-8140 | Form: LIQUID
Manufacturer: Uriel Pharmacy Inc.
Category: homeopathic | Type: HUMAN OTC DRUG LABEL
Date: 20260227

ACTIVE INGREDIENTS: GELSEMIUM SEMPERVIRENS ROOT 4 [hp_X]/1 mL; PSEUDOGNAPHALIUM LUTEOALBUM LEAF 4 [hp_X]/1 mL; ACONITUM NAPELLUS 6 [hp_X]/1 mL; ATROPA BELLADONNA 6 [hp_X]/1 mL; MANDRAGORA OFFICINARUM ROOT 6 [hp_X]/1 mL; TOXICODENDRON PUBESCENS LEAF 6 [hp_X]/1 mL; PENOXSULAM 10 [hp_X]/1 mL
INACTIVE INGREDIENTS: WATER; SODIUM CHLORIDE

Rhus Aconitum

PURPOSE

Use: Temporary relief of sore muscles.

INDICATIONS AND USAGE

FOR ORAL USE ONLY

DOSAGE AND ADMINISTRATION

Directions: Take the contents of one ampule under the tongue and hold for 30 seconds, then swallow. Follow inside instructions to open ampule.

Warnings:
NOT FOR INJECTION
Do not use if allergic to any ingredient. Consult a physician if symptoms worsen. If pregnant or nursing, consult a physician before use.
Claims based on traditional homeopathic practice, not accepted medical evidence. Not FDA evaluated.

KEEP OUT OF REACH OF CHILDREN.

ACTIVE INGREDIENT

Active Ingredients: Gelsemium (Yellow jasmine) 4X, Gnaphalium (Edelweiss) 4X, Aconitum (Monkshood) 6X, Atropa belladonna (Nightshade) 6X, Mandragora (Mandrake) 6X, Rhus tox (Sumac) 6X, Granite (Primitive rock containing quartz, feldspar, mica) 10X

Inactive Ingredients: Water, Salt

"prepared using rhythmical processes"

QUESTIONS

Questions? Call 866.642.2858 Uriel, East Troy, WI 53120 shopuriel.com